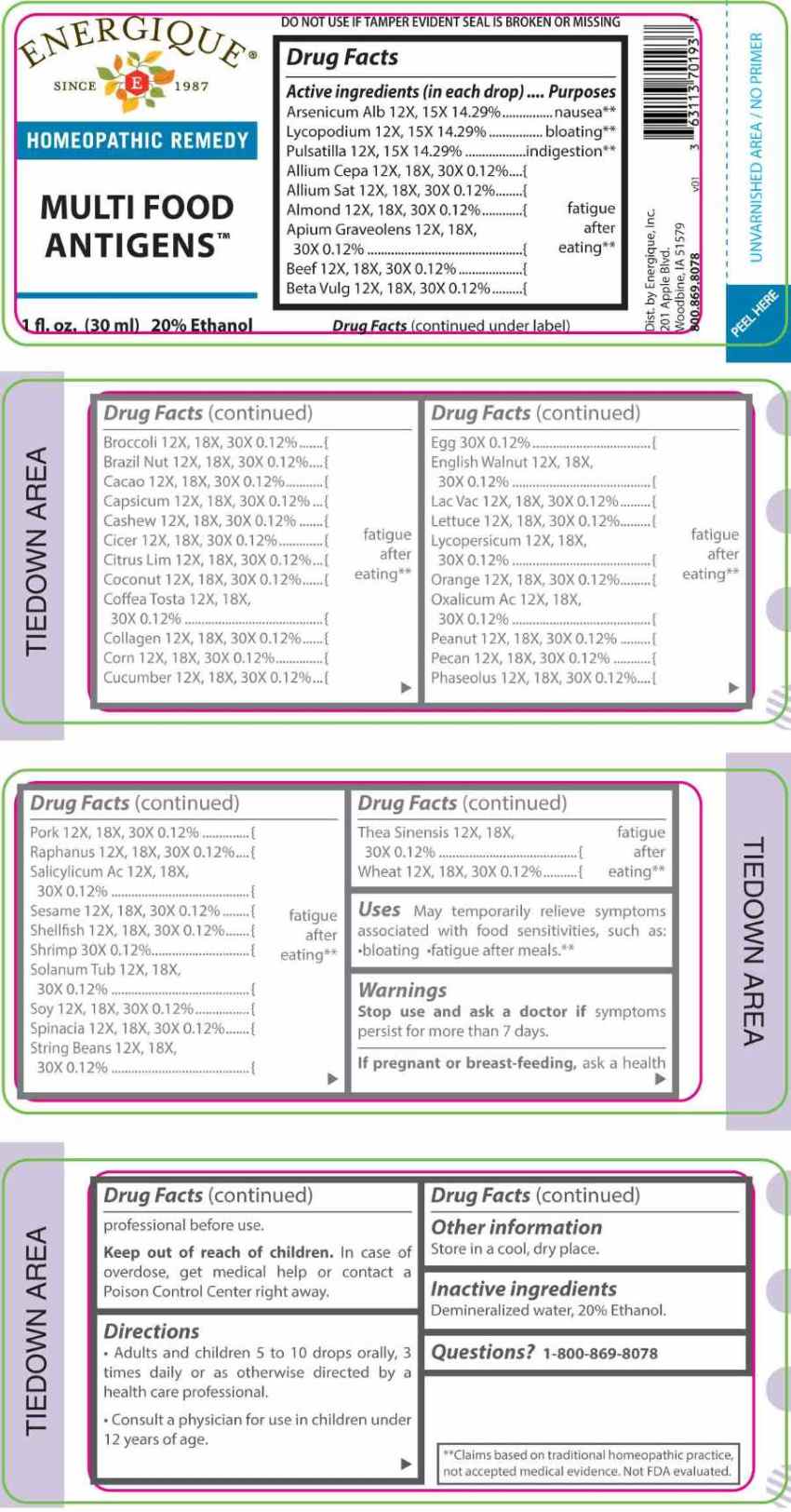 DRUG LABEL: Multi Food Antigens
NDC: 44911-0742 | Form: LIQUID
Manufacturer: Energique, Inc.
Category: homeopathic | Type: HUMAN OTC DRUG LABEL
Date: 20260106

ACTIVE INGREDIENTS: ARSENIC TRIOXIDE 12 [hp_X]/1 mL; LYCOPODIUM CLAVATUM SPORE 12 [hp_X]/1 mL; PULSATILLA PRATENSIS WHOLE 12 [hp_X]/1 mL; ONION 12 [hp_X]/1 mL; GARLIC 12 [hp_X]/1 mL; ALMOND 12 [hp_X]/1 mL; CELERY SEED 12 [hp_X]/1 mL; BETA VULGARIS WHOLE 12 [hp_X]/1 mL; BROCCOLI 12 [hp_X]/1 mL; BRAZIL NUT 12 [hp_X]/1 mL; COCOA 12 [hp_X]/1 mL; CAPSICUM 12 [hp_X]/1 mL; CASHEW 12 [hp_X]/1 mL; CHICKPEA 12 [hp_X]/1 mL; LEMON JUICE 12 [hp_X]/1 mL; COCONUT 12 [hp_X]/1 mL; COFFEA ARABICA SEED, ROASTED 12 [hp_X]/1 mL; HYDROLYSED BOVINE COLLAGEN (ENZYMATIC; 3500 MW) 12 [hp_X]/1 mL; CORN 12 [hp_X]/1 mL; CUCUMBER 12 [hp_X]/1 mL; ENGLISH WALNUT 12 [hp_X]/1 mL; SOYBEAN 12 [hp_X]/1 mL; BEEF HEART 12 [hp_X]/1 mL; PORK HEART 12 [hp_X]/1 mL; COW MILK 12 [hp_X]/1 mL; LETTUCE 12 [hp_X]/1 mL; SOLANUM LYCOPERSICUM WHOLE 12 [hp_X]/1 mL; ORANGE 12 [hp_X]/1 mL; OXALIC ACID DIHYDRATE 12 [hp_X]/1 mL; PEANUT 12 [hp_X]/1 mL; PECAN 12 [hp_X]/1 mL; KIDNEY BEAN 12 [hp_X]/1 mL; STRING BEAN 12 [hp_X]/1 mL; DAIKON 12 [hp_X]/1 mL; SALICYLIC ACID 12 [hp_X]/1 mL; SESAME SEED 12 [hp_X]/1 mL; SPINACH 12 [hp_X]/1 mL; SOLANUM TUBEROSUM WHOLE 12 [hp_X]/1 mL; GREEN TEA LEAF 12 [hp_X]/1 mL; NORTHERN QUAHOG 12 [hp_X]/1 mL; WHEAT 12 [hp_X]/1 mL; EGG 30 [hp_X]/1 mL; SHRIMP, UNSPECIFIED 30 [hp_X]/1 mL
INACTIVE INGREDIENTS: WATER; ALCOHOL

DRUG FACTS:

ACTIVE INGREDIENTS:

(in each drop) Arsenicum Album 12X, 15X, 14.29%, Lycopodium Clavatum 12X, 15X, 14.29%, Pulsatilla 12X, 15X 14.29%, Allium Cepa 12X, 18X, 30X 0.12%, Allium Sativum 12X, 18X, 30X 0.12%, Almond 12X, 18X, 30X 0.12%, Apium Graveolens 12X, 18X, 30X 0.12%, Beef 12X, 18X, 30X 0.12%, Beta Vulgaris 12X, 18X, 30X 0.12%, Broccoli 12X, 18X, 30X 0.12%, Brazil Nut 12X, 18X, 30X 0.12%, Cacao 12X, 18X, 30X 0.12%, Capsicum Annuum 12X, 18X, 30X 0.12%, Cashew 12X, 18X, 30X 0.12%, Cicer Arietinum 12X, 18X, 30X 0.12%, Citrus Limonum 12X, 18X, 30X 0.12%, Coconut 12X, 18X, 30X 0.12%, Coffea Tosta 12X, 18X, 30X 0.12%, Collagen 12X, 18X, 30X 0.12%, Corn 12X, 18X, 30X 0.12%, Cucumber 12X, 18X, 30X 0.12%, Egg 30X 0.12%, English Walnut 12X, 18X, 30X 0.12%, Lac Vaccinum 12X, 18X, 30X 0.12%, Lettuce 12X, 18X, 30X 0.12%, Lycopersicum Esculentum 12X, 18X, 30X 0.12%, Orange 12X, 18X, 30X 0.12%, Oxalicum Acidum 12X, 18X, 30X 0.12%, Peanut 12X, 18X, 30X 0.12%, Pecan 12X, 18X, 30X 0.12%, Phaseolus 12X, 18X, 30X 0.12%, Pork 12X, 18X, 30X 0.12%, Raphanus Sativus 12X, 18X, 30X 0.12%, Salicylicum Acidum 12X, 18X, 30X 0.12%, Sesame 12X, 18X, 30X 0.12%, Shellfish 12X, 18X, 30X 0.12%, Shrimp 30X 0.12%, Solanum Tuberosum 12X, 18X, 30X 0.12%, Soy 12X, 18X, 30X 0.12%, Spinacia 12X, 18X, 30X 0.12%, String Beans 12X, 18X, 30X 0.12%, Thea Sinensis 12X, 18X, 30X 0.12%, Wheat 12X, 18X, 30X 0.12%.

PURPOSE:

Arsenicum Album - nausea,** Lycopodium Clavatum - bloating,** Pulsatilla - indigestion,** Allium Cepa – fatigue after eating,** Allium Sativum - fatigue after eating,** Almond - fatigue after eating,** Apium Graveolens - fatigue after eating,** Beef - fatigue after eating,** Beta Vulgaris - fatigue after eating,** Broccoli - fatigue after eating,** Brazil Nut - fatigue after eating,** Cacao - fatigue after eating,** Capsicum Annuum - fatigue after eating,** Cashew - fatigue after eating,** Cicer Arietinum - fatigue after eating,** Citrus Limonum - fatigue after eating,** Coconut - fatigue after eating,** Coffea Tosta - fatigue after eating,** Collagen - fatigue after eating,** Corn - fatigue after eating,** Cucumber - fatigue after eating,** Egg - fatigue after eating,** English Walnut - fatigue after eating,** Lac Vaccinum - fatigue after eating,** Lettuce - fatigue after eating,** Lycopersicum Esculentum - fatigue after eating,** Orange - fatigue after eating,** Oxalicum Acidum - fatigue after eating,** Peanut - fatigue after eating,** Pecan - fatigue after eating,** Phaseolus - fatigue after eating,** Pork - fatigue after eating,** Raphanus Sativus - fatigue after eating,** Salicylicum Acidum - fatigue after eating,** Sesame - fatigue after eating,** Shellfish - fatigue after eating,** Shrimp - fatigue after eating,** Solanum Tuberosum - fatigue after eating,** Soy - fatigue after eating,** Spinacia - fatigue after eating,** String Beans - fatigue after eating,** Thea Sinensis - fatigue after eating,** Wheat - fatigue after eating,**

**Claims based on traditional homeopathic practice, not accepted medical evidence. Not FDA evaluated.

USES:

May temporarily relieve symptoms associated with food sensitivities, such as:

•bloating •fatigue after meals.**

**Claims based on traditional homeopathic practice, not accepted medical evidence. Not FDA evaluated.

WARNINGS:

Stop use and ask a doctor if symptoms persist for more than 7 days.

If pregnant or breast-feeding, ask a health professional before use.

Keep out of reach of children. In case of overdose, get medical help or contact a Poison Control Center right away.

DO NOT USE IF TAMPER EVIDENT SEAL IS BROKEN OR MISSING

Store in a cool, dry place.

KEEP OUT OF REACH OF CHILDREN:

In case of overdose, get medical help or contact a Poison Control Center right away.

DIRECTIONS:

• Adults and children 5 to 10 drops orally, 3 times daily or as otherwise directed by a health care professional.

• Consult a physician for use in children under 12 years of age.

INACTIVE INGREDIENTS:

Demineralized water, 20% Ethanol.

QUESTIONS:

Dist. by Energique, Inc.

201 Apple Blvd

Woodbine, IA 51579

800.869.8078

PACKAGE LABEL DISPLAY:

ENERGIQUE
SINCE 1987
HOMEOPATHIC REMEDY
MULTI FOOD ANTIGENS
1 fl. oz. (30 ml)